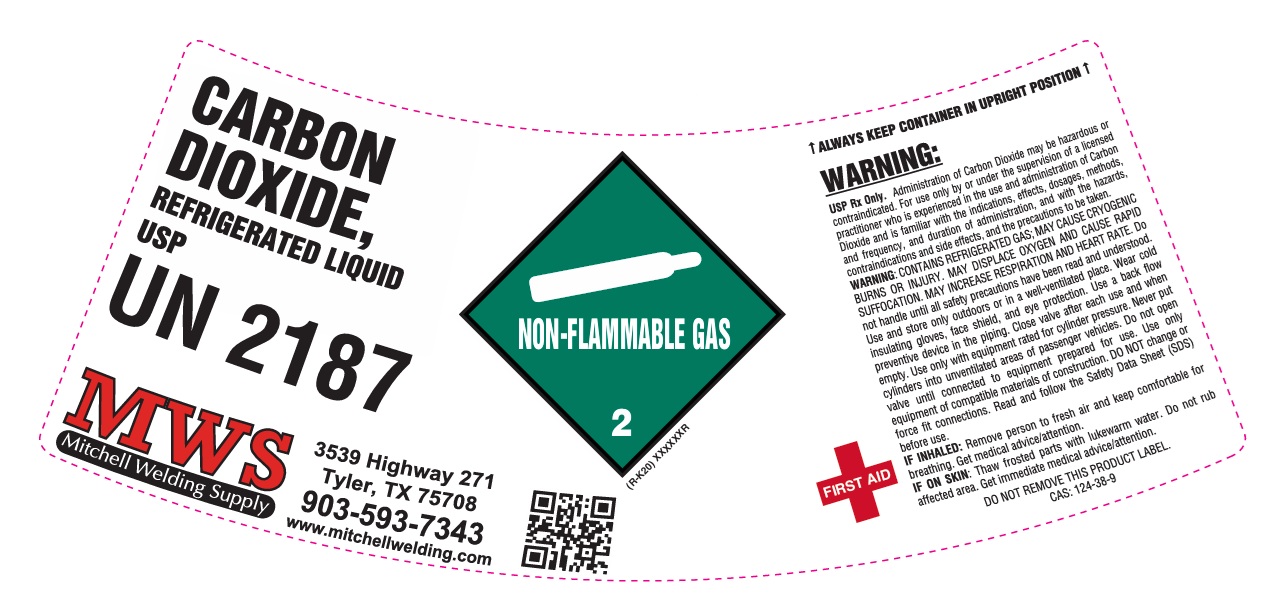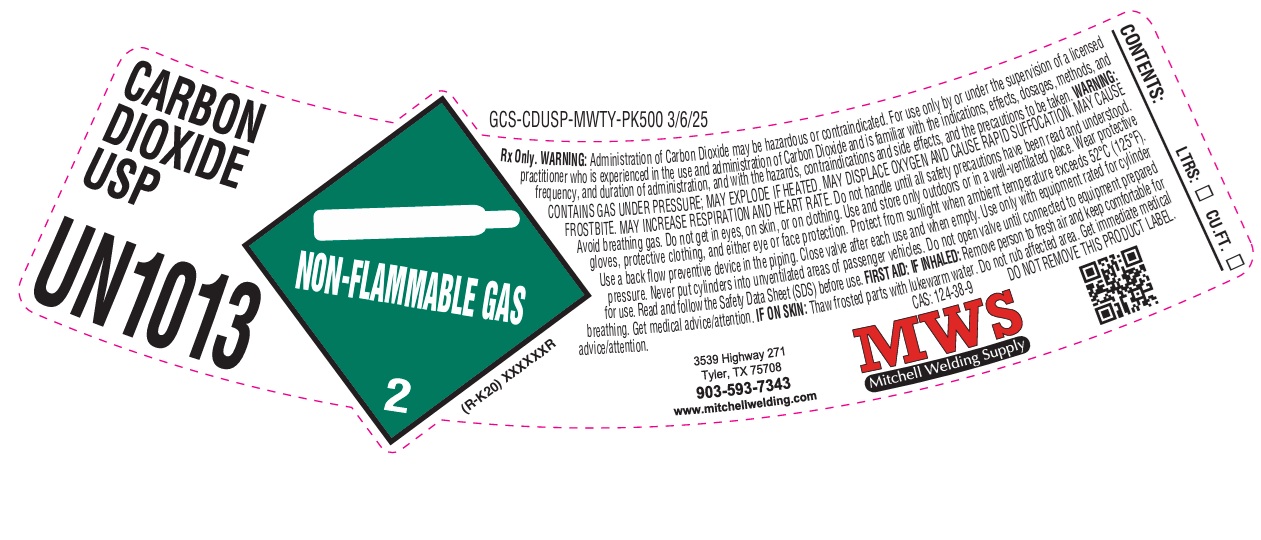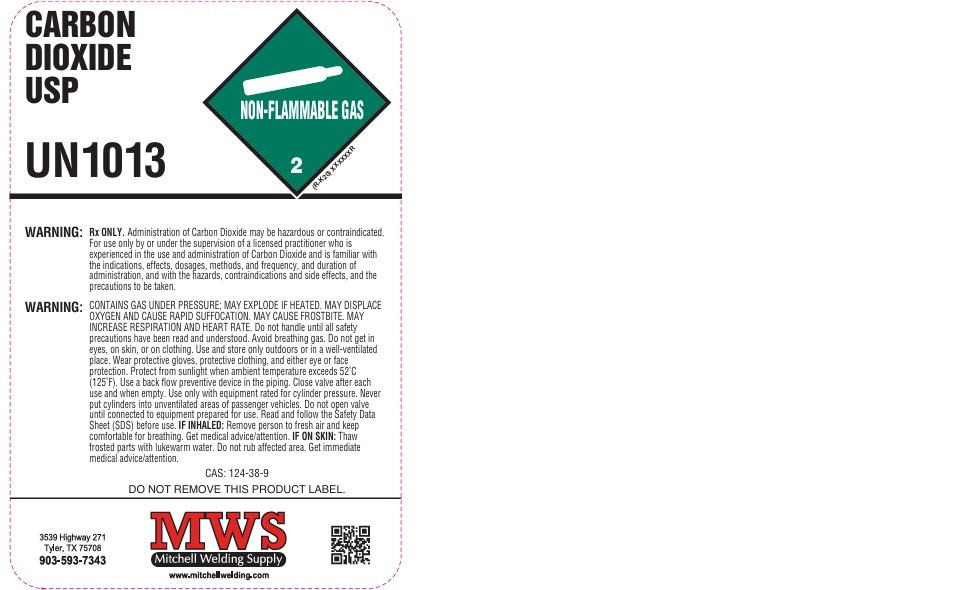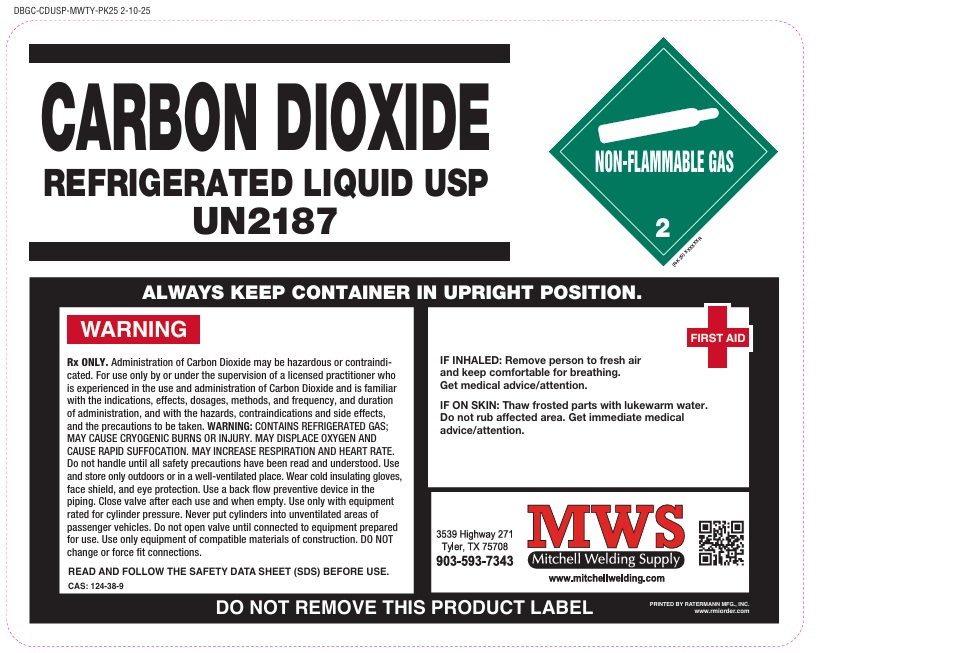 DRUG LABEL: Carbon Dioxide
NDC: 72276-004 | Form: GAS
Manufacturer: MITCHELL WELDING SUPPLY	
Category: prescription | Type: HUMAN PRESCRIPTION DRUG LABEL
Date: 20251120

ACTIVE INGREDIENTS: CARBON DIOXIDE 990 mL/1 L

Carbon Dioxide

PACKAGE LABEL

CARBON DIOXIDE USP

UN1013

Rx Only. WARNING: Administration of Carbon Dioxide may be hazardous or contraindicated. For use only by or under the supervision of a licensed practitioner who is experienced in the use and administration of Carbon Dioxide and is familiar with the indications, effects, dosages, methods, and frequency, and duration of administration, and with the hazards, contraindications and side effects, and the precautions to be taken. WARNING: CONTAINS GAS UNDER PRESSURE; MAY EXPLODE IF HEATED. MAY DISPLACE OXYGEN AND CAUSE RAPID SUFFOCATION. MAY CAUSE FROSTBITE. MAY INCREASE RESPIRATION AND HEART RATE. Do not handle until all safety precautions have been read and understood. Avoid breathing gas. Do not get in eyes, on skin, or on clothing. Use and store only outdoors or in a well-ventilated place. Wear protective gloves, protective clothing, and either eye or face protection. Protect from sunlight when ambient temperature exceeds 52 C (125 F). Use a back flow preventive device in the piping. Close after each use and when empty. Use only with equipment rated for cylinder pressure. Never put cylinders into unventilated areas of passenger vehicles. Do not open valve until connected to equipment prepared for use. Read and follow the Safety Data Sheet (SDS0 before use. FIRST AID: IF INHALED: Remove person to fresh air and keep comfortable for breathing. Get medical advice/attention. IF ON SKIN: Thaw frosted parts with lukewarm water. Do not rub affected area. Get immediate medical advice/attention.

CAS: 124-38-9 DO NOT REMOVE THIS PRODUCT LABEL.

3539 Highway 271

Tyler, TX 75708

903-593-7343

www.mitchellwelding.com

MWS

Mitchell Welding Supply

CONTENTS: LTRS: CU.FT.

PACKAGE LABEL

CARBON DIOXIDE

REFRIGERATED LIQUID USP

UN2187

ALWAYS KEEP CONTAINER IN UPRIGHT POSITION.

WARNING

Rx ONLY. Administration of Carbon Dioxide may be hazardous or contraindicated. For use only by or under the supervision of a licensed practitioner who is experienced in the use and administration of Carbon Dioxide and is familiar with the indications, effects, dosages, methods, and frequency, and duration of administration, and with the hazards, contraindications and side effects, and the precautions to be taken. WARNING: CONTAINS REFRIGERATED GAS; MAY CAUSE CRYOGENIC BURNS OR INJURY. MAY DISPLACE OXYGEN AND CAUSE RAPID SUFFOCATION. MAY INCREASE RESPIRATION AND HEART RATE. Do not handle until all safety precautions have been read and understood. Use and store only outdoors or in a well-ventilated place. Wear cold insulating gloves, face shield, and eye protection. Use a back flow preventive device in the piping. Close valve after each use and when empty. Use only with equipment rated for cylinder pressure. Never put cylinders into unventilated areas of passenger vehicles. Do not open valve until connected to equipment prepared for use. Use only equipment of compatible materials of construction. DO NOT change or force fit connections.

READ AND FOLLOW THE SAFETY DATA SHEET (SDS) BEFORE USE.

CAS: 124-38-9

FIRST AID

IF INHALED: Remove person to fresh air and keep comfortable for breathing. Get medical advice/attention.

IF ON SKIN: Thaw frosted parts with lukewarm water. Do not rub affected area. Get immediate medical advice/attention.

3539 Highway 271

Tyler, TX 75708

903-593-7343

MWS

Mitchell Welding Supply

www.mitchellwelding.com

PACKAGE LABEL

CARBON DIOXIDE USP

UN1013

WARNING: Rx ONLY. Administration of Carbon Dioxide may be hazardous or contraindicated. For use only by or under the supervision of a licensed practitioner who is experienced in the use and administration of Carbon Dioxide and is familiar with the indications, effects, dosages, methods, and frequency, and duration of administration, and with the hazards, contraindications and side effects, and the precautions to be taken.

WARNING: CONTAINS GAS UNDER PRESSURE; MAY EXPLODE IF HEATED. MAY DISPLACE OXYGEN AND CAUSE RAPID SUFFOCATION. MAY CAUSE FROSTBITE. MAY INCREASE RESPIRATION AND HEART RATE. Do not handle until all safety precautions have been read and understood. Avoid breathing gas. Do not get in eyes, on skin, or on clothing. Use and store only outdoors or in a well-ventilated place. Wear protective gloves, protective clothing, and either eye or face protection. Protect from sunlight when ambient temperature exceeds 52 C (125 F). Use a back flow preventive device in the piping. Close valve after each use and when empty. Use only with equipment rated for cylinder pressure. Never put cylinders into unventilated areas of passenger vehicles. Do not open valve until connected to equipment prepared for use. Read and follow the Safety Data Sheet (SDS) before use. IF INHALED: Remove person to fresh air and keep comfortable for breathing. Get medical advice/attention. IF ON SKIN: Thaw frosted parts with lukewarm water. Do not rub affected area. Get immediate medical advice/attention.

CAS: 124-38-9

DO NOT REMOVE THIS PRODUCT LABEL.

3539 Highway 271

Tyler, TX 75708

903-593-7343

MWS

Mitchell Welding Supply

www.mitchellwelding.com

PACKAGE LABEL

CARBON DIOXIDE, REFRIGERATED LIQUID USP

UN2187

MWS

Mitchell Welding Supply

3539 Highway 271

Tyler, TX 75708

903-593-7343

www.mitchellwelding.com

ALWAYS KEEP CONTAINER IN UPRIGHT POSITION

WARNING:

USP Rx Only. Administration of Carbon Dioxide may be hazardous or contraindicated. For use only by or under the supervision of a licensed practitioner who is experienced in the use and administration of Carbon Dioxide and is familiar with the indications, effects, dosages, methods, and frequency, and duration of administration, and with the hazards, contraindications and side effects, and the precautions to be taken.

WARNING: CONTAINS REFRIGERATED GAS; MAY CAUSE CRYOGENIC BURNS OR INJURY. MAY DISPLACE OXYGEN AND CAUSE RAPID SUFFOCATION. MAY INCREASE RESPIRATION AND HEART RATE. Do not handle until all safety precautions have been read and understood. Use and store only outdoors or in a well-ventilated place. Wear cold insulating gloves, face shield, and eye protection. Use a back flow preventive device in the piping. Close valve after each use and when empty. Use only with equipment rated for cylinder pressure. Never put cylinders into unventilated areas of passenger vehicles. Do not open valve until connected to equipment prepared for use. Use only equipment of compatible materials of construction. DO NOT change or force fit connections. Read and follow the Safety Data Sheet (SDS) before use.

FIRST AID IF INHALED: Remove person to fresh air and keep comfortable for breathing. Get medical advice/attention.

IF ON SKIN: Thaw frosted parts with lukewarm water. Do not rub affected area. Get immediate medical advice/attention.

DO NOT REMOVE THIS PRODUCT LABEL.

CAS: 124-38-9